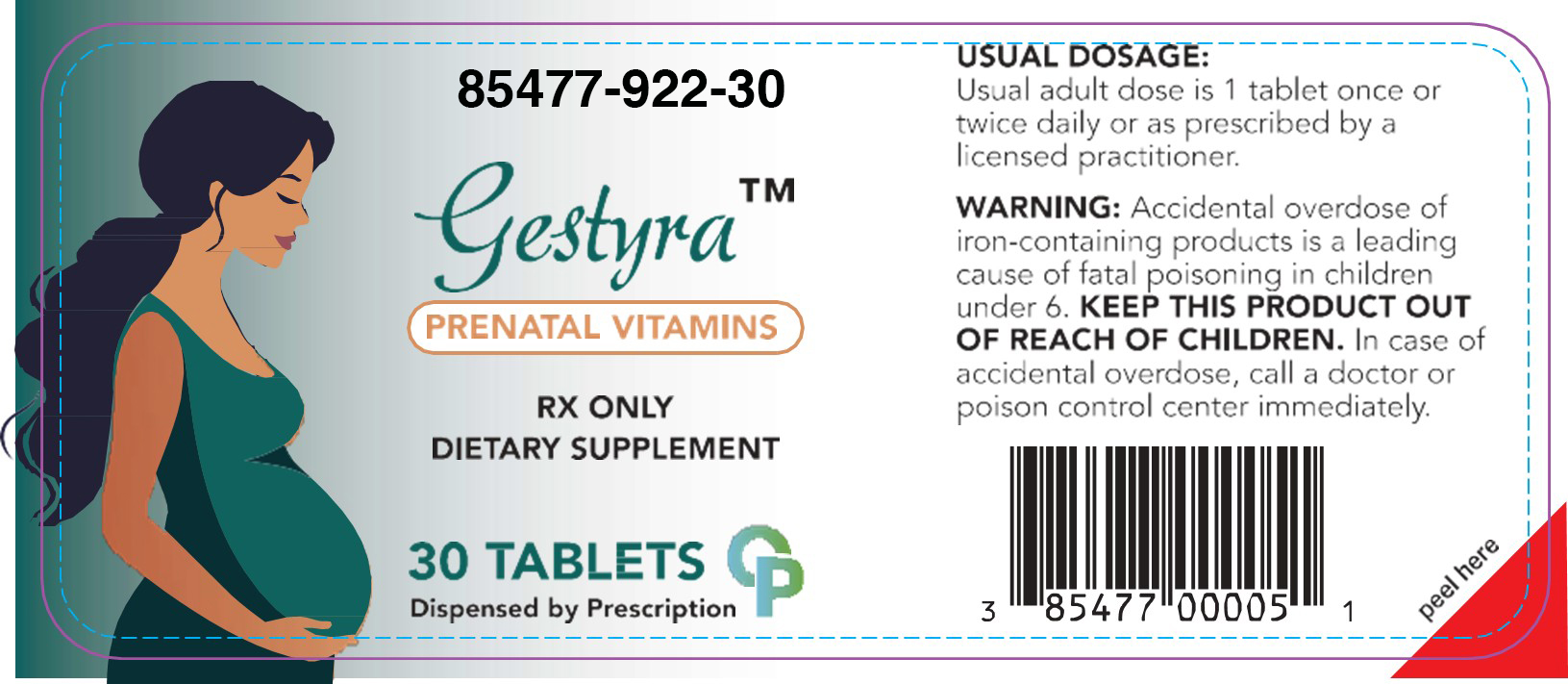 DRUG LABEL: Gestyra
NDC: 85477-922 | Form: TABLET
Manufacturer: Oncora Pharma LLC
Category: prescription | Type: HUMAN PRESCRIPTION DRUG LABEL
Date: 20251230

ACTIVE INGREDIENTS: ASCORBIC ACID 125 mg/1 1; CHOLECALCIFEROL 12.5 ug/1 1; THIAMINE 1.4 mg/1 1; PYRIDOXAL PHOSPHATE ANHYDROUS 2.5 mg/1 1; FOLIC ACID 1 mg/1 1; METHYLCOBALAMIN 1000 ug/1 1; CALCIUM CARBONATE 200 mg/1 1; FERROUS GLUCONATE 13 mg/1 1; POTASSIUM IODIDE 0.15 mg/1 1
INACTIVE INGREDIENTS: MAGNESIUM STEARATE; CELLULOSE, MICROCRYSTALLINE; SILICON DIOXIDE

Prenatal
Rx Only

DESCRIPTION

Each Tablet Contains:

Amount per Tablet

Vitamin C (as ascorbic acid) ............................................................................... 125 mg

Vitamin D (as cholecalciferol) ............................................................................. 12.5 mcg

Thiamine (as hydrochloride) ............................................................................... 1.4 mg

Vitamin B6 (as pyridoxal•S•phosphate) ...................................... ....................... 2.5 mg

Folic Acid ............................................................................................................ 1 mg

Vitamin B12 (as methylcobalamin)...................................................................... 1,000 mcg

Calcium (from calcium carbonate) ...................................................................... 200 mg

Iron (as ferrous gluconate) ................................................................................. 13 mg

Iodine (as potassium iodide............................................................................... 150 mcg

OTHER INGREDIENTS: Microcrystalline Cellulose, Magnesium Stearate, Silia, Glycerin, Vanilla Extract

INDICATIONS AND USAGE

Prenatal and Postnatal prescriptive Folic Acid

WARNINGS

WARNING: Accidental overdose of iron-containing products is a leading cause of fatal poisoning in children under age 6. KEEP THIS PRODUCT OUT OF REACH OF CHILDREN. In case of accidental overdose, call a doctor or Poison Control Center immediately.

PRECAUTIONS

Call your licensed medical practitioner about side effects.

DOSAGE AND ADMINISTRATION

Usual adult dose is 1 tablet once or twice daily or as prescribed by a licensed practitioner.

HOW SUPPLIED

Bottles of 30: 85477-922-30

Storage

KEEP THIS AND ALL MEDICATION OUR OF THE REACH OF CHILDREN.